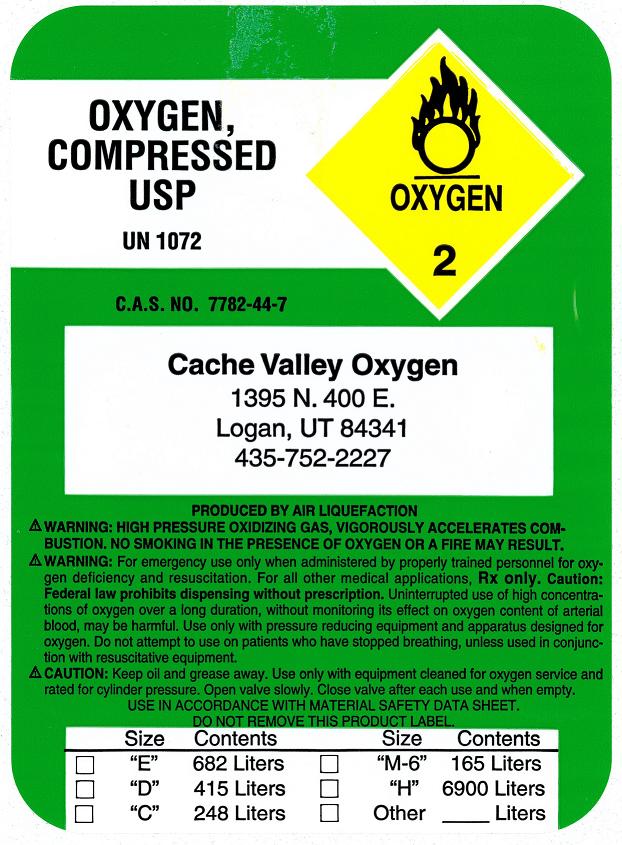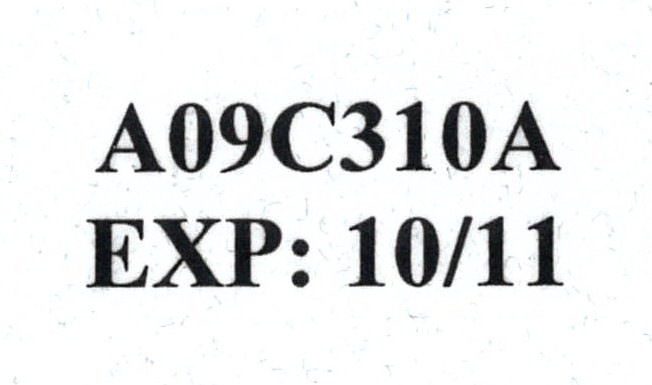 DRUG LABEL: Oxygen
NDC: 66390-0001 | Form: GAS
Manufacturer: Cache Valley Oxygen
Category: prescription | Type: HUMAN PRESCRIPTION DRUG LABEL
Date: 20091112

ACTIVE INGREDIENTS: Oxygen 99 L/100 L

Oxygen